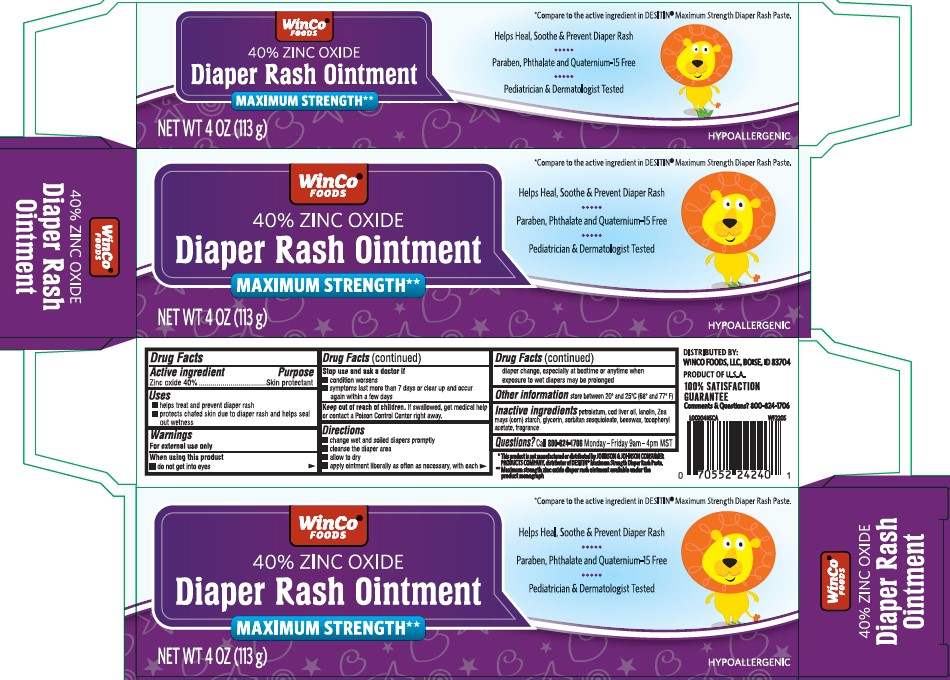 DRUG LABEL: Diaper Rash
NDC: 67091-020 | Form: OINTMENT
Manufacturer: WinCo Foods, LLC
Category: otc | Type: HUMAN OTC DRUG LABEL
Date: 20260212

ACTIVE INGREDIENTS: ZINC OXIDE 400 mg/1 g
INACTIVE INGREDIENTS: PETROLATUM; COD LIVER OIL; LANOLIN; STARCH, CORN; GLYCERIN; SORBITAN SESQUIOLEATE; YELLOW WAX; .ALPHA.-TOCOPHEROL ACETATE

Winco 020.002/020AC-AD
Diaper Rash Ointment 40% Zinc Oxide

Active Ingredient

Zinc oxide 40%

Purpose

Skin protectant

uses

- helps treat and prevent diaper rash
- protects chafed skin due to diaper rash and helps seal out wetness

Warnings

For external use only

When using this product

do not get into eyes

Stop use and ask a doctor if

- condition worsens
- symptoms last more than 7 days or clear up and occur again within a few days

Keep out of reach of children.

If swallowed, get medical help or contact a Poison Control Center right away.

Directions

- change wet and soiled diapers promptly
- cleanse the diaper area
- allow to dry
- apply ointment liberally as often as necessary, with each diaper change, especially at bedtime or anytime when exposure to wet diapers may be prolonged

Other information

store between 20⁰ and 25⁰C (68⁰ and 77⁰F)

Inactive ingredients

petrolatum, cod liver oil, lanolin, Zea mays (corn) starch, glycerin, sorbitan sesquioleate, beeswax, tocopheryl acetate, fragrance

Questions?

Call 800-824-1706 Monday-Friday 9am-4pm MST

Disclaimer

*This product is not manufactured or distributed by Johnson & Johnson Consumer Products Company, distributor of Destin®Maximum Strength Daiper Rash Paste.

**Maximum strength zinc oxide diaper rash ointment available under the product monograph

Adverse reaction

DISTRIBUTED BY

WINCO Foods, LLC, Boise, ID 83704

Product of U.S.A.

100% Satisfaction Guarantee

Comments & Questions? 800-824-1706

principal display panel

WinCo®Foods

40% Diaper Rach Ointment

Maximum Strength**

*Compate to the active ingredient in DESTIN®Maximum Strength Diaper Rash Paste.

Helps Heal, Soothe & Prevent Diaper Rash

Paraben, Phthalate and Quaternium-15 Free

Pediatrician & Dermatologist Tested

HYPOALLERGENIC

Net WT 4 OZ (113 g)